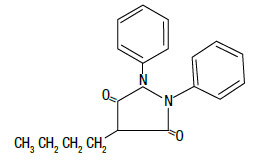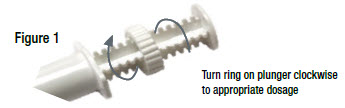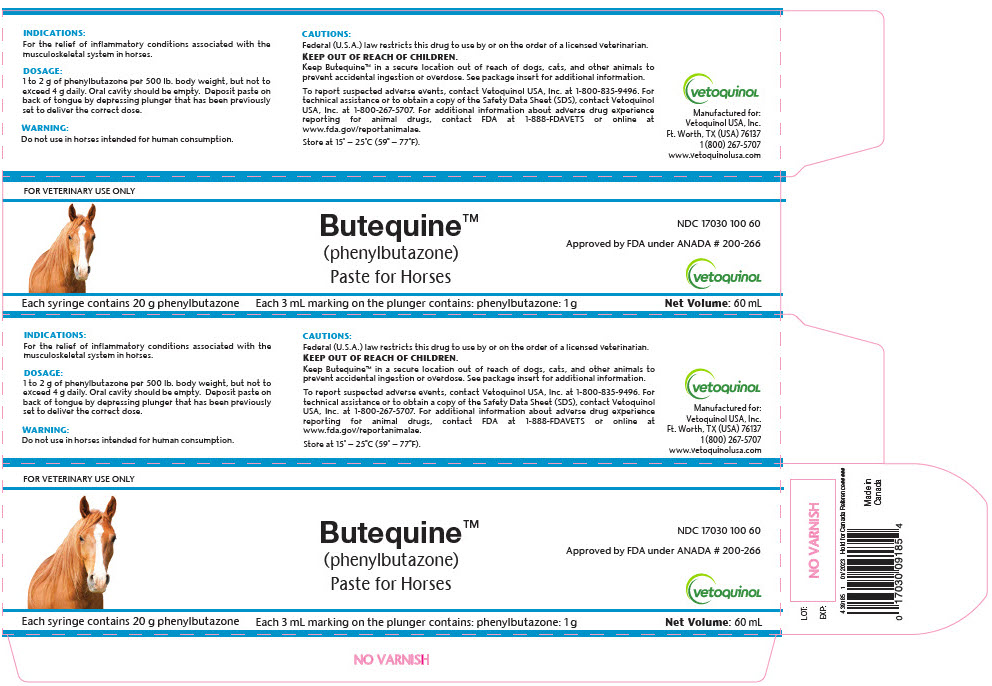 DRUG LABEL: BUTEQUINE
NDC: 17030-100 | Form: PASTE
Manufacturer: Vetoquinol USA, Inc.
Category: animal | Type: PRESCRIPTION ANIMAL DRUG LABEL
Date: 20231116

ACTIVE INGREDIENTS: PHENYLBUTAZONE 1 g/3 mL

BUTEQUINE™ (phenylbutazone)
Paste for Horses

NDC 17030 100 60
Approved by FDA under ANADA # 200-266

For Veterinary Use Only

DESCRIPTION

DESCRIPTION: Butequine™ paste is a synthetic, non-hormonal anti-inflammatory, antipyretic compound useful in the management of inflammatory conditions. The apparent analgesic effect is probably related mainly to the compound's anti-inflammatory properties. Chemically, phenylbutazone is 4-butyl-1, 2-diphenyl-3, 5-pyrazolidinedione. It is a pyrazalone derivative, entirely unrelated to the steroid hormones, and has the following structural formula:

VETERINARY INDICATIONS

INDICATIONS: For the relief of inflammatory conditions associated with the musculoskeletal system in horses.

CONTRAINDICATIONS

CONTRAINDICATIONS: Use with caution in patients who have a history of drug allergy.

WARNINGS

WARNING: Do not use in horses intended for human consumption.

PRECAUTIONS

PRECAUTIONS: Stop medication at the first sign of gastrointestinal upset, jaundice, or blood dyscrasia. Authenticated cases of agranulocytosis associated with the drug have occurred in man; fatal reactions, although rare, have been reported in dogs after long-term therapy. To guard against the possibility, conduct routine blood counts at weekly intervals during the early phase of therapy and at intervals of two weeks thereafter. Any significant fall in the total white blood cell count, relative decrease in granulocytes, or black or tarry stools should be regarded as a signal for immediate cessation of therapy and institution of appropriate counter-measures. In the treatment of inflammatory conditions associated with infections, specific anti-infective therapy is required.

DOSAGE AND ADMINISTRATION

ADMINISTRATION AND DOSAGE: Orally – 1 to 2 g of phenylbutazone per 500 lb. (227 kg) of body weight daily. Do not exceed 4 g daily. Use a relatively high dose for the first 48 hours, then reduce gradually to a maintenance dose. Maintain lowest dose capable of producing desired clinical response.

Guidelines to Successful Therapy:

1. Important - To avoid overdosing and to ensure the correct first dose, move ring on plunger to the appropriate dosage position before administration (see Figure 1). The edge of the ring closest to the syringe barrel should be aligned to the gram/dosage mark on the plunger.
2. When administering Butequine™ paste the oral cavity should be empty. Set ring on plunger to deliver the appropriate dosage based on weight (see Figure 1). Deposit paste on the back of tongue by depressing plunger.
3. Use a relatively high dose for the first 48 hours (not to exceed 4 g daily), then reduce gradually to a maintenance dose. Maintain lowest dose capable of producing desired clinical response.
4. Response to Butequine™ paste therapy is prompt, usually occuring within 24 hours. If no significant clinical response is evident after 5 days, reevaluate diagnosis and therapeutic approach.
5. Many chronic conditions will respond to Butequine™ paste therapy, but discontinuance of treatment may result in recurrence of symptoms.

STORAGE AND HANDLING

STORAGE: Store at 15°-25°C (59°-77°F).

HOW SUPPLIED: Syringes containing 20 g phenylbutazone.

KEEP OUT OF REACH OF CHILDREN

Keep Butequine™ in a secure location out of reach of dogs, cats, and other animals to prevent accidental ingestion or overdose.

CAUTION: Federal (U.S.A.) law restricts this drug to use by or on the order of a licensed veterinarian.

CONTACT INFORMATION:

To report suspected adverse events, contact Vetoquinol USA, Inc. at 1-800-835-9496. For technical assistance or to obtain a copy of the Safety Data Sheet (SDS), contact Vetoquinol USA, Inc. at 1-800-267-5707. For additional information about adverse drug experience reporting for animal drugs, contact FDA at 1-888-FDAVETS or online at www.fda.gov/reportanimalae

Manufactured for:
Vetoquinol USA, Inc.
Ft. Worth, TX (USA) 76137
www.vetoquinolusa.com

439185
Rev 01/2023
Hold for Canada
Reference #####

PRINCIPAL DISPLAY PANEL - 60 mL Syringe Carton

FOR VETERINARY USE ONLY

Butequine™
(phenylbutazone)
Paste for Horses

NDC 17030 100 60

Approved by FDA under ANADA # 200-266

vetoquinol

Each syringe contains 20 g phenylbutazone

Each 3 mL marking on the plunger contains: phenylbutazone: 1 g

Net Volume: 60 mL